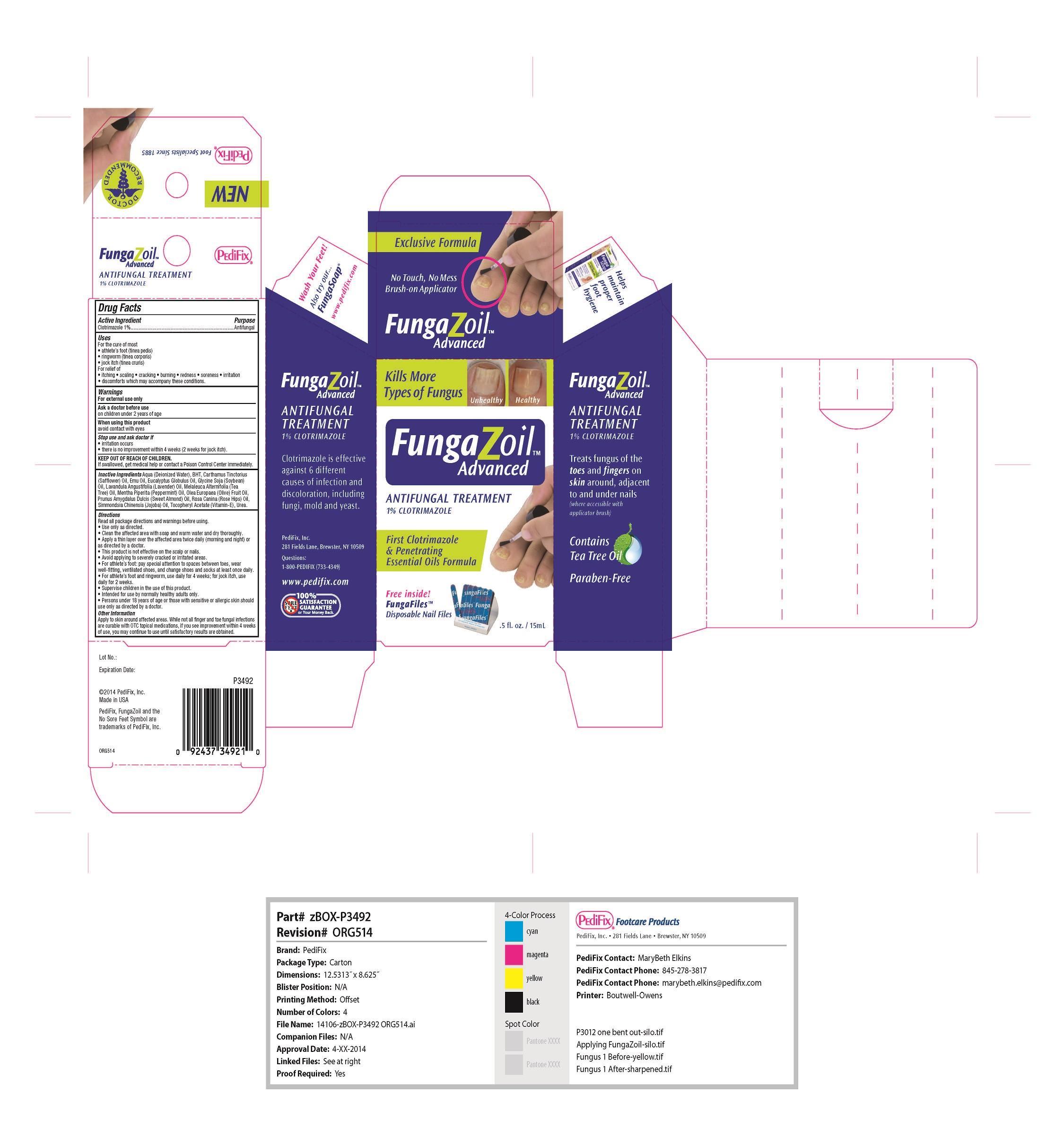 DRUG LABEL: FungaZoil Advanced
NDC: 68927-3492 | Form: LIQUID
Manufacturer: Pedifix
Category: otc | Type: HUMAN OTC DRUG LABEL
Date: 20140612

ACTIVE INGREDIENTS: CLOTRIMAZOLE 10 mg/1 mL
INACTIVE INGREDIENTS: .ALPHA.-TOCOPHEROL; WATER; BUTYLATED HYDROXYTOLUENE; SAFFLOWER OIL; EMU OIL; EUCALYPTUS GLOBULUS LEAF; SOYBEAN OIL; LAVENDER OIL; TEA TREE OIL; PEPPERMINT OIL; OLIVE OIL; ALMOND OIL; ROSA CANINA FRUIT OIL; JOJOBA OIL; UREA

FungaZoil Advanced

Warnings

For external use only

Ask a doctor before use on children under 2 years of age

When using this product avoid contact with eyes

Stop use and as doctor if irritation occurs, there is no improvement within 4 weeks (2 weeks for jock itch)

If swallowed, get medical help or contact a Poison control center immediately.

Active Ingredient

Clotrimazole 1%

Inactive ingredients

Aqua (Deionized Water), BHT, Carthamus Tinctorius (Safflower) Oil, Emu Oil, Eucalyptus Globulus Oil, Glycine Soja (Soybean) Oil, Lavandula Angustifolia (Lavender) Oil, Melaleuca Alternifolia (Tea Tree) Oil, Mentha Piperita (Peppermint) Oil, Olea Europaea (Olive) Fruit Oil, Prunus Amygdalus Dulcis (Sweet Almond) Oil, Rosa Canina (Rose Hips) Oil, Simmondsia Chinensis (Jojoba) Oil, Tocopheryl Acetate (Vitamin- E), Urea.

KEEP OUT OF REACH OF CHILDREN

Purpose

Antifungal

Uses

For the cure of most
• athlete’s foot (tinea pedis)
• ringworm (tinea corporis)
• jock itch (tinea cruris) For relief of
• itching • scaling • cracking • burning • redness • soreness • irritation
• discomforts which may accompany these conditions.

Directions

Read all package directions and warnings before using.
• Use only as directed.
• Clean the affected area with soap and warm water and dry thoroughly.
• Apply a thin layer over the affected area twice daily (morning and night) or as directed by a doctor.
• This product is not effective on the scalp or nails.
• Avoid applying to severely cracked or irritated areas.
• For athlete’s foot: pay special attention to spaces between toes, wear well-fitting, ventilated shoes, and change shoes and socks at least once daily.
• For athlete’s foot and ringworm, use daily for 4 weeks; for jock itch, use daily for 2 weeks.
• Super vise children in the use of this product.
• Intended for use by normally healthy adults only.
• Persons under 18 years of age or those with sensitive or allergic skin should use only as directed by a doctor.
Other Information
Apply to skin around affected areas. While not all finger and toe fungal infections are curable with OTC topical medications, if you see improvement within 4 weeks of use, you may continue to use until satisfactory results are obtained.